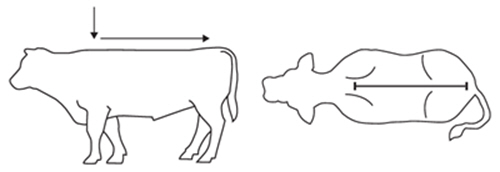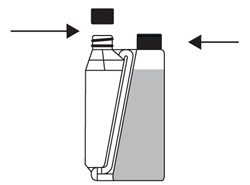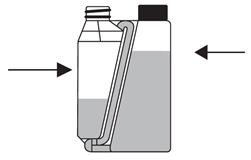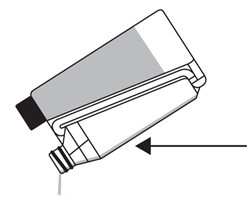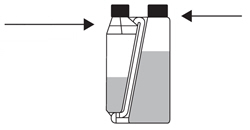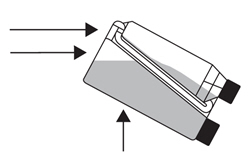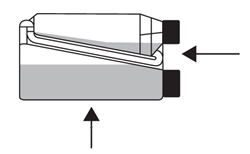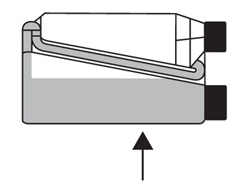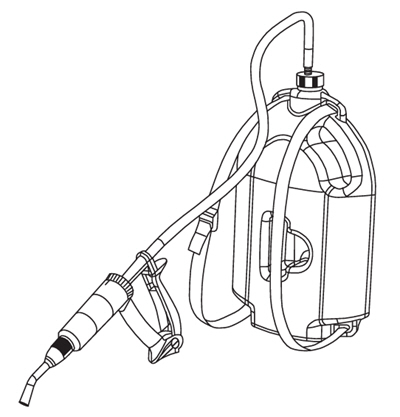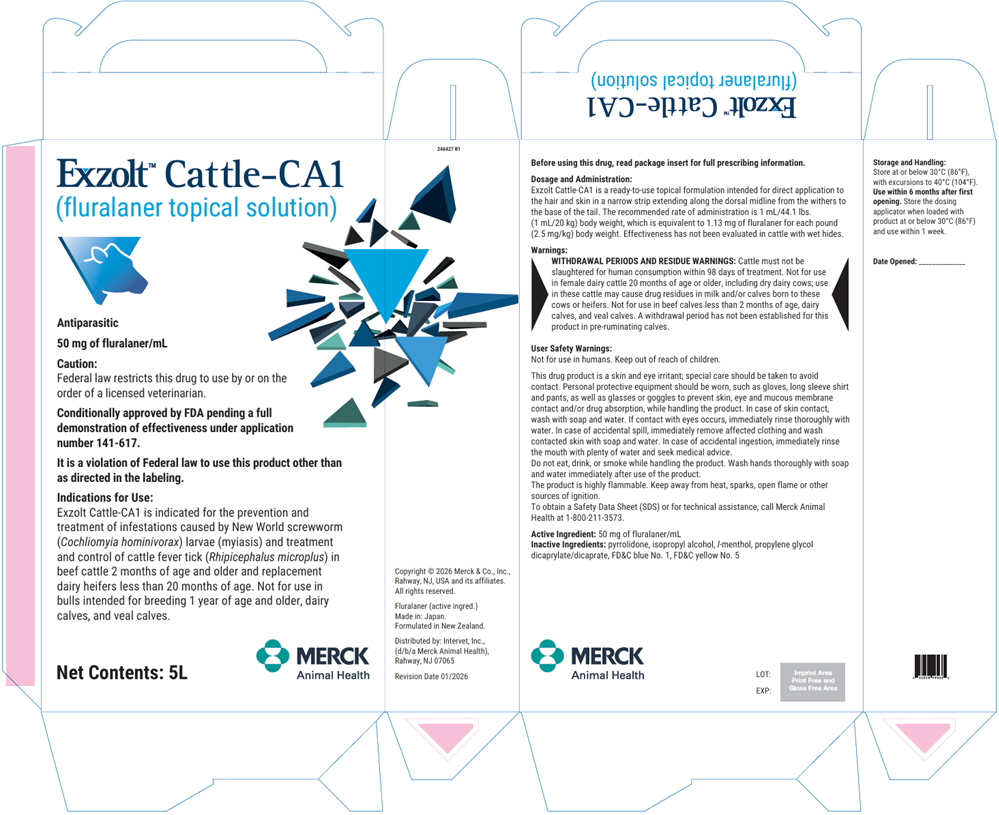 DRUG LABEL: EXZOLT CATTLE-CA1
NDC: 0061-1442 | Form: SOLUTION
Manufacturer: Merck Sharp & Dohme Corp.
Category: animal | Type: PRESCRIPTION ANIMAL DRUG LABEL
Date: 20260130

ACTIVE INGREDIENTS: FLURALANER 50 mg/1 L
INACTIVE INGREDIENTS: PROPYLENE GLYCOL DICAPRYLATE; FD&C BLUE NO. 1; FD&C YELLOW NO. 5 FREE ACID; ISOPROPYL ALCOHOL; PYRROLIDONE; LEVOMENTHOL

Exzolt™ Cattle-CA1
(fluralaner topical solution)

Antiparasitic

50 mg of mL/fluralaner

Caution:

Federal law restricts this drug to use by or on the order of a licensed veterinarian.

Conditionally approved by FDA pending a full demonstration of effectiveness under application number 141-617.

It is a violation of Federal law to use this product other than as directed in the labeling.

Description:

Exzolt Cattle-CA1 (fluralaner topical solution) contains fluralaner, an antiparasitic of the isoxazoline class. Each mL of Exzolt Cattle-CA1 contains 50 mg of fluralaner.

The chemical name of fluralaner is (±)-4-[5-(3,5-dichlorophenyl)-5-(trifluoromethyl)-4,5-dihydroisoxazol-3-yl]-2-methyl-N-[2-oxo-2-(2,2,2-trifluoroethylamino)ethyl]benzamide.

Inactive Ingredients: pyrrolidone, isopropyl alcohol, l-menthol, propylene glycol dicaprylate/dicaprate, FD&C blue No. 1, FD&C yellow No. 5

Indications for Use:

Exzolt Cattle-CA1 is indicated for the prevention and treatment of infestations caused by New World screwworm (Cochliomyia hominivorax) larvae (myiasis) and treatment and control of cattle fever tick (Rhipicephalus microplus) in beef cattle 2 months of age and older and replacement dairy heifers less than 20 months of age. Not for use in bulls intended for breeding 1 year of age and older, dairy calves, and veal calves.

Dosage and Administration:

Exzolt Cattle-CA1 is a ready-to-use topical formulation intended for direct application to the hair and skin in a narrow strip extending along the dorsal midline from the withers to the base of the tail (see Figure 1). The recommended rate of administration is 1 mL/44.1 lbs. (1 mL/20 kg) body weight, which is equivalent to 1.13 mg of fluralaner for each pound (2.5 mg/kg) body weight. Effectiveness has not been evaluated in cattle with wet hides.

Recommended site of administration:

Figure 1: Recommended location for the topical application in a narrow strip along the dorsal midline from the withers to the base of the tail.

Administration of the product with 250 mL and 1L bottles with built-in dosing chamber:

To ensure administration of a correct dose, body weight should be determined as accurately as possible, and accuracy of the dosing volume should be checked before administration. Round the dose up to the nearest volume increment on the dosing chamber, which goes up in 2.5 mL increments.

The table below can be consulted to assist in the calculation of the appropriate volume which must be applied based on the weight of animal being treated.

Body Weight (Pounds) | Dose Volume (mL)
220 | 5
330 | 7.5
440 | 10
550 | 12.5
660 | 15
770 | 17.5
880 | 20
990 | 22.5
1100 | 25
1320 [Add 2.5 mL for each 110 pounds above 1320 pounds of body weight.] | 30

Practice the Administration and Overfill Reduction Instructions a few times to become familiar with operating the package before dosing animals.

Step 1 On first use remove cap and peelable seal from the dosing chamber. |  | Do not remove cap from the bottle.
Step 2 Dosing chamber |  | Hold the bottle upright and at eye level while slowly and gently squeezing the bottle to fill the dosing chamber to the selected mark.
Step 3 |  | Pour the measured volume on the dorsal midline from withers to the base of the tail. Application to a small area should be avoided.

A small amount of liquid will remain on the walls of the chamber, but the chamber is calibrated to account for this.

Avoid squeezing the container section while the solution is poured from the dosing chamber.

If the dosing chamber is overfilled follow the Overfill Reduction Instructions below:

Step 1
Re-apply cap to dosing chamber and tighten.

Confirm the cap is tight.

Step 2
Transfer Tube Air Pocket

Tilt the bottle to allow an air pocket to form at the beginning of the transfer tube inside the bottle.

Step 3

Transfer Tube

Hold the bottle horizontally to allow product to cover the end of the transfer tube inside the dosing chamber.

Step 4

Squeeze and release the bottle repeatedly.

Product will return to the bottle through the transfer tube.

Administration of the product with 5L bottle with an applicator device:

These bottles are designed for use with the Simcro Breaze™ Applicator Device (30 mL). This applicator device and delivery tubing (sold separately by Simcro as a kit) should be used with the 5L bottle. The 5L bottle is supplied with spigot cap attached to dip tube for its use with the applicator device. A strap is also included for use of the 5L bottle as a backpack.

To ensure administration of a correct dose, body weight should be determined as accurately as possible, and accuracy of the dosing volume should be checked before administration. Round the dose up to the nearest volume increment on the applicator device, which goes up in 1 mL increments.

The table below can be consulted to assist in the calculation of the appropriate volume which must be applied based on the weight of animal being treated.

Body Weight (Pounds) | Dose Volume (mL)
220 | 5
440 | 10
660 | 15
880 | 20
1100 | 25
1320 [Add 1 mL for each 44 pounds above 1320 pounds of body weight.] | 30

Assembly, Disassembly and Cleaning Instructions for the 5L bottle with applicator device:

Step 1

Follow the applicator device manufacturer's assembly directions. Connect one end of the delivery tubing to the connection point on the dosing applicator.

Step 2

Remove the transit cap and protection seal from the 5L bottle and replace with spigot cap attached to dip tube. Tighten spigot cap to bottle and attach other end of delivery tubing to the spigot cap. Do not discard the transit cap until the contents of the 5L bottle are completely used. Please refer to Figure 2 for the assembled 5L bottle with applicator device.

Step 3

Keeping the 5L bottle in an upright position, gently prime the applicator device per the included manufacturer's instructions, checking for leaks. With the applicator device in an upward position, expel all visible air from the barrel and confirm that product is visibly expressed from the tip of the applicator device so that it is free of any residual air.

Step 4

Follow the applicator device manufacturer's directions for adjusting the dose.

Step 5

When the interval between uses of the applicator device is expected to exceed 1 week, take off the entire spigot assembly (delivery tubing connected to the spigot cap with attached dip tube while still connected to the applicator device), from the 5L bottle. Return any unused product remaining in the applicator device and in the delivery tubing back into the 5L bottle. Raise the spigot cap with dip tube attached and place the tip of the applicator device into the 5L bottle. Discharge the remaining product from the spigot assembly into the bottle. Place the transit cap onto the 5L bottle to close it. Submerge the dip tube in warm, soapy water. Flush warm soapy water through the delivery tubing and through the applicator device, followed by flushing them with clean water and allowing them to dry. Once dry, store the entire dosing assembly (applicator device, delivery tubing, spigot cap with attached dip tube) in a safe, clean place until next use. Refer to the manufacturer's directions for maintenance of the applicator.

Figure 2. 5L bottle and applicator device with tubing.

Warnings:

RESIDUE WARNING

WITHDRAWAL PERIODS AND RESIDUE WARNINGS: Cattle must not be slaughtered for human consumption within 98 days of treatment. Not for use in female dairy cattle 20 months of age or older, including dry dairy cows; use in these cattle may cause drug residues in milk and/or calves born to these cows or heifers. Not for use in beef calves less than 2 months of age, dairy calves, and veal calves. A withdrawal period has not been established for this product in pre-ruminating calves.

SAFE HANDLING WARNING

User Safety Warnings:

Not for use in humans. Keep out of reach of children.

This drug product is a skin and eye irritant; special care should be taken to avoid contact. Personal protective equipment should be worn, such as gloves, long sleeve shirt and pants, as well as glasses or goggles to prevent skin, eye and mucous membrane contact and/or drug absorption, while handling the product. In case of skin contact, wash with soap and water. If contact with eyes occurs, immediately rinse thoroughly with water. In case of accidental spill, immediately remove affected clothing and wash contacted skin with soap and water. In case of accidental ingestion, immediately rinse the mouth with plenty of water and seek medical advice.

Do not eat, drink, or smoke while handling the product. Wash hands thoroughly with soap and water immediately after use of the product.

The product is highly flammable. Keep away from heat, sparks, open flame or other sources of ignition.

To obtain a Safety Data Sheet (SDS) or for technical assistance, call Merck Animal Health at 1-800-211-3573.

Contact Information:

Contact Merck Animal Health at 1-800-211-3573 or https://www.merck-animal-health-usa.com.

To report suspected adverse drug experiences, contact Livestock Technical Service at 1-800-211-3573. For additional information about reporting adverse drug experiences for animal drugs, contact FDA at 1-888-FDA-VETS or https://www.fda.gov/reportanimalae.

Clinical Pharmacology:

Mechanism of Action

Fluralaner belongs to the class of isoxazoline-substituted benzamide derivatives. Fluralaner is an inhibitor of the arthropod nervous system. The mode of action of fluralaner is the antagonism of the ligand-gated chloride channels (gamma-aminobutyric acid (GABA)-receptor and glutamate-receptor).

Pharmacokinetics

The pharmacokinetic properties of a single 2.5 mg/kg dose of Exzolt Cattle-CA1 administered topically along the dorsal midline from the withers to the base of the tail to cattle that were not restricted from grooming are presented in Table 1 (n = 12).

Table 1: Mean (± standard deviation) plasma pharmacokinetic parameters of total fluralaner [Although total fluralaner (R+S) is reported, the S enantiomer is more abundant and active than the R] after a single topical administration of Exzolt Cattle-CA1 in male and female cattle in warm conditions (54 – 98 °F)
Parameter (units) | Estimate
Cmax (ng/mL) | 127 ± 82.2
Tmax [Median and range] (day) | 5 (4 – 12)
AUC(0-56) (day*ng/mL) | 1570 ± 1220
AUCinf (day*ng/mL) | 1590 ± 1230
t½ (day) | 8.48 ± 1.84
Cmax = maximum plasma concentration
Tmax = time to maximum plasma concentration
AUC(0-56) represents the AUC from day 0 to day 56
AUCinf = area under the curve from the time of dosing extrapolated to infinity
t½ = half-life

Target Animal Safety

Margin of Safety:

In a margin of safety study, Exzolt Cattle-CA1 was well tolerated in 32 six to seven month old healthy beef cattle (16 males and 16 females). Study animals were administered 3.7, 11.1, or 18.5 mg/kg body weight (1X, 3X, and 5X the maximum anticipated labeled dose) of Exzolt Cattle-CA1 by topical application three times 42 days apart (Days 0, 42, and 84). Cattle in the control group (0X) were treated with green dyed sterile saline at a dose volume similar to the 5X treated group. General health observations were conducted twice daily from acclimation to the end of the 98-day study. Variables measured periodically throughout the study for each animal were body weight; physical examinations; neurological examinations; analysis of blood for hematology, clinical chemistry, coagulation, and toxicokinetics; fecal and urine analysis; and feed and water consumption. All animals were necropsied at the end of the study for gross and histopathological examination and select organs were weighed.

Test article-related application site reactions, including skin flaking/scurfing and scabbing were observed. These findings were dose-dependent in both incidence and severity. Reactions in the 1X animals appeared after the second administration. These reactions in the 1X group were cosmetic in nature and did not require treatment.

Female Reproductive Safety:

In a reproductive safety study, Exzolt Cattle-CA1 was well tolerated in 200 healthy beef cows between the ages of 3 to 11 years old. Study animals were administered 11.1 mg fluralaner/kg body weight (3X the maximum labeled dose) of Exzolt Cattle-CA1 by a single topical application once during breeding (estrus; before timed-artificial insemination), early in the 1st trimester of pregnancy, during the mid-1st trimester of pregnancy, or in the 3rd trimester of pregnancy. Cattle in the control group (0X) were treated with green dyed sterile saline at a dose volume similar to the treated groups (3X). General health observations were conducted twice daily from acclimation to the end of the study at 30±2 days postpartum. Variables measured at start of acclimation and at the end of the study for each animal were body weight (including prior to each dosing) and physical examinations (including at parturition for offspring). Reproductive safety parameters included conception rate, abortion rate, calving rate, live births, stillborn calves, perinatal death, premature deliveries, neonatal death, dystocia, ability of calf to stand, walk and suckle, and abnormalities. Three stillbirths and one premature delivery were observed in animals in the control group. One stillbirth associated with dystocia and one premature delivery were documented in cows treated with Exzolt Cattle-CA1.

Six abortions occurred across three of the Exzolt Cattle-CA1 treated groups (2 out of 31 cows in the estrus-treated group; 2 out of 34 cows in the early first trimester-treated group; 2 out of 27 cows in the mid first trimester-treated group). One calf was found dead within 24 hours of birth in an Exzolt Cattle-CA1 treated cow. These events were considered to occur at rates typical for the source herd and unlikely to be test article related. Not for use in bulls intended for breeding over 1 year of age, as reproductive safety has not been evaluated.

Reasonable Expectation of Effectiveness

A reasonable expectation of effectiveness may be demonstrated based on evidence such as, but not limited to, pilot data in the target species or studies from published literature.

Exzolt Cattle-CA1 is conditionally approved pending a full demonstration of effectiveness. Additional information for Conditional Approvals can be found at www.fda.gov/animalca. A reasonable expectation of effectiveness for Exzolt Cattle-CA1 for the prevention and treatment of infestations caused by New World screwworm (Cochliomyia hominivorax) larvae (myiasis) and treatment and control of cattle fever tick (Rhipicephalus microplus) in beef cattle 2 months of age and older and replacement dairy heifers less than 20 months of age is based on results from the following foreign studies conducted in Australia, Brazil, and South Africa.

A. New World Screwworm (NWS) (Cochliomyia hominivorax) Three effectiveness studies utilizing natural NWS infestations conducted in Brazil in 2018 are described below:
  1. Support for a prevention indication: This study evaluated prevention of New World Screwworm (NWS) myiasis in a surgical wound created seven days after treatment administration. Animals received either a placebo (n=6) or Exzolt Cattle-CA1 (n=6) on Day -7. Seven days later, two surgical incisions were made on each side of the body at the shoulder. Animals were housed outside to facilitate natural infestation of the wounds with NWS. Cattle were monitored twice daily for 10 days post-incision to assess the presence of eggs and larvae. A single topical application of Exzolt Cattle-CA1 at the dose of 2.5 mg/kg provided 100% prevention against myiasis for the length of the study.
  2. Support for a prevention indication: This study evaluated prevention of NWS myiasis in a castration wound created on the day of treatment with either a placebo (n=15) or Exzolt Cattle-CA1 (n=15). Animals were housed outside to facilitate natural infestation of the wounds with NWS. Cattle were monitored daily for 14 days post-surgery to assess the presence of eggs, larvae, and the progress of wound healing. A single topical administration of Exzolt Cattle-CA1 at the dose of 2.5 mg/kg provided 100% prevention against myiasis for up to 14 days following castration.
  3. Support for a therapeutic indication: This study evaluated the effectiveness of the product to treat a wound already infested with NWS. A surgical wound was created and left exposed to facilitate natural infestation with NWS. Three days later, after confirming the presence of live larvae, animals were treated topically once with either a placebo (n=12) or Exzolt Cattle-CA1 (n=12). A single topical administration of Exzolt Cattle-CA1 at the dose of 2.5 mg/kg achieved 90.9% effectiveness by the second day post-treatment and reached 100% effectiveness by the third day. No myiasis in treated animals was observed up to day 5.
B. Cattle Fever Tick (Rhipicephalus microplus)
  Three dose confirmation studies conducted in Brazil and South Africa and a rain exposure study conducted in Brazil utilizing induced infestations of R. microplus were evaluated. These studies were conducted between 2018 and 2021. In each study, animals were individually housed and randomly assigned to control and Exzolt Cattle-CA1-treated groups. Exzolt Cattle-CA1-treated groups received a single administration at the dose of 2.5 mg/kg. A total of thirty animals were treated with Exzolt Cattle-CA1 across these four studies. The product demonstrated 100% effectiveness within the first week after Exzolt Cattle-CA1 administration. Length of consistent 100% persistent effectiveness ranged from 39 days to approximately 110 days post-treatment.
  Thirteen field effectiveness studies conducted in Brazil and Australia utilizing natural infestations of R. microplus were evaluated. These studies were conducted between 2017 and 2023. In each study, animals were grouped housed and randomly assigned to control and Exzolt Cattle-CA1-treated groups. Exzolt Cattle-CA1-treated groups received a single administration at the dose of 2.5 mg/kg. Approximately 220 animals were treated with Exzolt Cattle-CA1 across these thirteen studies. The product demonstrated 100% effectiveness within the first week after Exzolt Cattle-CA1 administration. Length of consistent 100% persistent effectiveness ranged from 28 days to 70 days post-treatment.
C. Rain exposure study
  One study was conducted to evaluate the impact of simulated rainfall post-treatment on the effectiveness of Exzolt Cattle-CA1 with cattle artificially infested with R. microplus. A total of 30 cattle (cross-bred beef bulls) were randomized to one of five groups with six animals each: Groups A, B, C, and D were treated with Exzolt Cattle-CA1 (2.5 mg/kg) and Group E with saline (equivalent volume). Groups A, B, and C were exposed to simulated rainfall at the following post-treatment timepoints: 6 hr, 12 hr, and 24 hr, respectively. Groups D and E had no exposure to rain. Percent effectiveness of Exzolt Cattle-CA1 was 100% in Groups A, B, C, and D up to 77 days. Rain exposure as early as 6 hr post-treatment did not affect the therapeutic or persistent effectiveness of Exzolt Cattle-CA1 in beef cattle.

How Supplied:

Exzolt Cattle-CA1 is available in 250 mL, 1L, and 5L bottles.

Storage and Handling:

Store at or below 30°C (86°F), with excursions to 40°C (104°F). Use within 6 months after first opening. Store the dosing applicator when loaded with product at or below 30°C (86°F) and use within 1 week.

Distributed by: Intervet, Inc., (d/b/a Merck Animal Health), Rahway, NJ 07065

Formulated in New Zealand

Copyright © 2026 Merck & Co., Inc., Rahway, NJ, USA and its affiliates. All rights reserved.

Revision Date 01/2026

246425 R1

PRINCIPAL DISPLAY PANEL - 5L Bottle Carton

Exzolt™ Cattle-CA1
(fluralaner topical solution)

Antiparasitic

50 mg of fluralaner/mL

Caution:
Federal law restricts this drug to use by or on the
order of a licensed veterinarian.

Conditionally approved by FDA pending a full
demonstration of effectiveness under application
number 141-617.

It is a violation of Federal law to use this product other than
as directed in the labeling.

Indications for Use:
Exzolt Cattle-CA1 is indicated for the prevention and
treatment of infestations caused by New World screwworm
(Cochliomyia hominivorax) larvae (myiasis) and treatment
and control of cattle fever tick (Rhipicephalus microplus) in
beef cattle 2 months of age and older and replacement
dairy heifers less than 20 months of age. Not for use in
bulls intended for breeding 1 year of age and older, dairy
calves, and veal calves.

Net Contents: 5L

MERCK
Animal Health